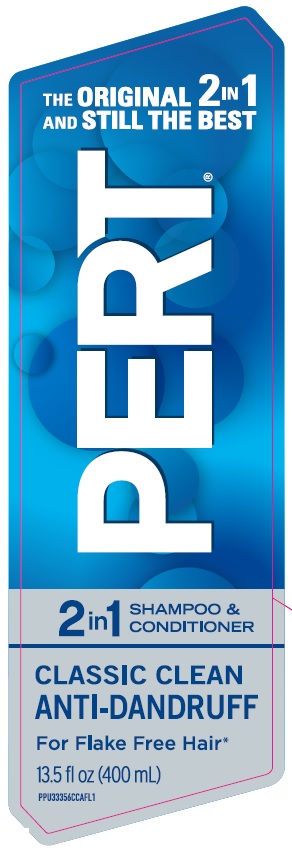 DRUG LABEL: Pert Plus 2 in 1
NDC: 81277-801 | Form: SHAMPOO, SUSPENSION
Manufacturer: TCP HRB Holdings
Category: otc | Type: HUMAN OTC DRUG LABEL
Date: 20240101

ACTIVE INGREDIENTS: PYRITHIONE ZINC 1 g/100 mL
INACTIVE INGREDIENTS: GLYCOL DISTEARATE; WATER; COCO MONOETHANOLAMIDE; DIMETHICONE; COCAMIDOPROPYL BETAINE; FRAGRANCE 13576; SODIUM CHLORIDE; GUAR HYDROXYPROPYLTRIMONIUM CHLORIDE (1.7 SUBSTITUENTS PER SACCHARIDE); GLYCERIN; SODIUM CITRATE; SODIUM BENZOATE; SODIUM LAURETH SULFATE; SODIUM LAURYL SULFATE; METHYLCHLOROISOTHIAZOLINONE; METHYLISOTHIAZOLINONE; FD&C BLUE NO. 1; D&C YELLOW NO. 10; CARBOMER COPOLYMER TYPE B (ALLYL PENTAERYTHRITOL CROSSLINKED)

Pert Plus 2 in 1 Shampoo and Conditioner Anti-Dandruff

THE ORIGINAL 2 IN ONE AND STILL THE BEST

PERT

CLASSIC CLEAN ANTI-DANDRUFF

for flake free hair*

Drug Facts

Active Ingredient

Pyrithione Zinc 1%

Purpose

Antidandruff

INDICATIONS AND USAGE

Use Controls the symptoms of dandruff

Warnings

For external use only

When using this product

- avoid contact with eyes. If contact occurs, rinse eyes thoroughly with water.

Stop use and ask a doctor if

- condition worsens or does not improve after regular use of this product as directed.

Keep out of reach of children. If swallowed, get medical help or contact a Poison Control Center right away.

Directions

- For best results, use at least twice a week or as directed by a doctor.
- Shake before use.
- Gently massage into wet hair and scalp, lather and rinse. Repeat if desired.

INACTIVE INGREDIENT

Inactive ingredients: water(aqua), sodium laureth sulfate, sodium lauryl sulfate, cocamidopropyl betaine, glycerin, cocamide MEA, dimethicone, glycol distearate, fragrance(parfum), guar hydroxypropyltrimonium chloride, sodium citrate, acrylates/C10-30 alkyl acrylate crosspolymer, sodium benzoate, sodium chloride, methylchloroisothiazolinone, methylisothiazolinone, yellow 10(CI47005), blue 1 (CI42090).

Questions or Comments?

1-800-575-7960 www.pert.com

*visible flakes; with regular use.

Distributed by HRB Brands, LLC

Westport, CT 06880

pert.com • 1-800-575-7960

Pert is a registered trademark of TCP HOT IP LLC.

Made in Canada.

PACKAGE LABEL

THE ORIGINAL 2 IN 1 AND STILL THE BEST

PERT®

2 IN 1 SHAMPOO & CONDITIONER

CLASSIC CLEAN

ANTI-DANDRUFF

For Flake Free Hair*

13.5 fl oz (400 mL)